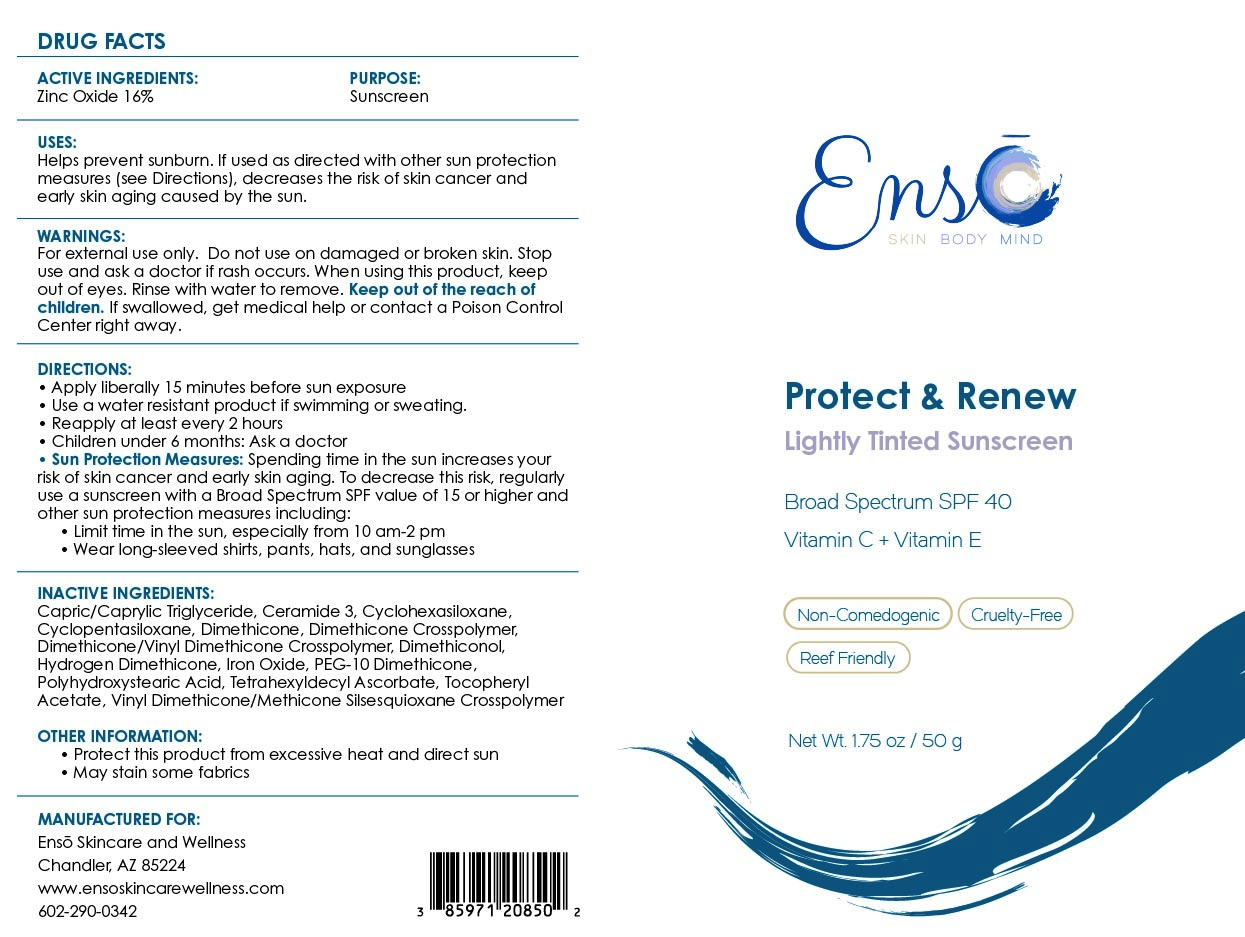 DRUG LABEL: Protect and Renew
NDC: 85971-208 | Form: CREAM
Manufacturer: ENSO SKINCARE & WELLNESS LLC
Category: otc | Type: HUMAN OTC DRUG LABEL
Date: 20251217

ACTIVE INGREDIENTS: ZINC OXIDE 160 mg/1 g
INACTIVE INGREDIENTS: CAPRYLIC/CAPRIC TRIGLYCERIDE; CYCLOHEXASILOXANE; CI 77492; CI 77499; PEG-10 DIMETHICONE (600 CST); POLYHYDROXYSTEARIC ACID (2300 MW); VINYL DIMETHICONE/METHICONE SILSESQUIOXANE CROSSPOLYMER; CERAMIDE 3; CI 77491; ALPHA-TOCOPHEROL ACETATE; CYCLOPENTASILOXANE; DIMETHICONOL (2000 CST); DIMETHICONE/VINYL DIMETHICONE CROSSPOLYMER (SOFT PARTICLE); DIMETHICONE CROSSPOLYMER; HYDROGEN DIMETHICONE (20 CST); TETRAHEXYLDECYL ASCORBATE

Active Ingredients:

Zinc Oxide 16%

Purpose:

Sunscreen

Uses:

Helps Prevent Sunburn. If used as directed with other sun protection measures (see “Directions”), decreases the risk of skin cancer and early skin aging caused by the sun.

Warnings:

For external use only. Do not use on broken or damaged skin. Stop use and ask a doctor if rash occurs. When using this product, keep out of eyes. Rinse with water to remove. Keep out of reach of children. If swallowed, get medical help or contact a poison control center right away.

Warnings:

Keep out of reach of children

Directions:

Apply liberally 15 minutes before sun exposure. Use a water-resistant product if swimming or sweating. Reapply at least every 2 hours. Children under 6 months: Ask a doctor. Sun Protection Measures: Spending time in the sun increases your risk of skin cancer and early skin aging. To decrease this risk, regularly use a sunscreen with a Broad-Spectrum SPF value of 15 or higher and other sun protection measures including: Limit time in the sun, especially from 10 a.m. - 2 p.m. Wear long-sleeved shirts, pants, hats and sunglasses.

Inactive Ingredients:

Capric/Caprylic Triglyceride, Ceramide 3, Cyclohexasiloxane, Cyclopentasiloxane, Dimethicone, Dimethicone Crosspolymer, Dimethicone/Vinyl Dimethicone Crosspolymer, Dimethiconol, Iron Oxide, Hydrogen Dimethicone, PEG-10 Dimethicone, Polyhydroxystearic Acid, Tetrahexyldecyl Ascorbate, Tocopheryl Acetate, Vinyl Dimethicone/Methicone Silsesquioxane Crosspolymer

Other Information:

- Protect this product from excessive heat and direct sun
- May stain some fabrics